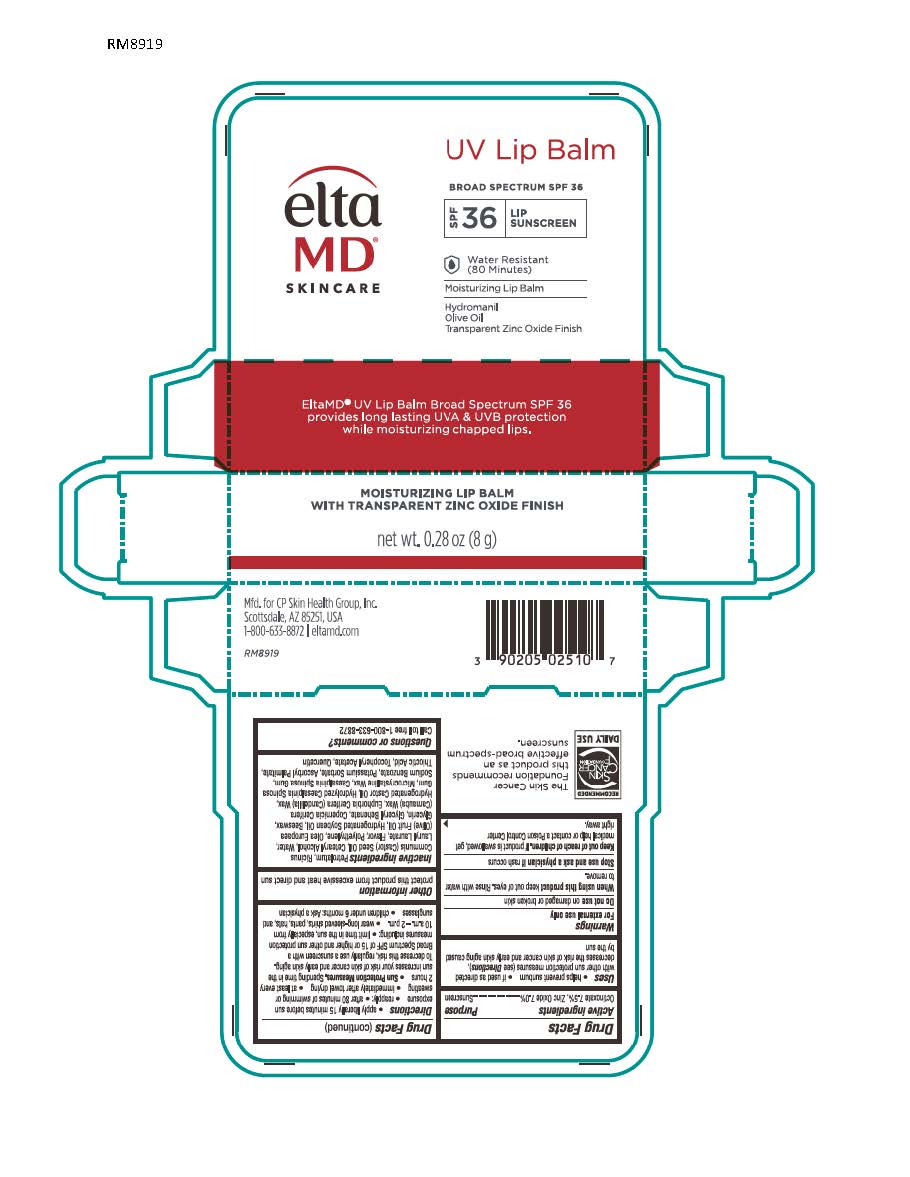 DRUG LABEL: EltaMD UV Lip Balm SPF31
NDC: 72043-2510 | Form: LOTION
Manufacturer: CP Skin Health, Inc
Category: otc | Type: HUMAN OTC DRUG LABEL
Date: 20240125

ACTIVE INGREDIENTS: ZINC OXIDE 50 g/1000 g; OCTINOXATE 75 g/1000 g
INACTIVE INGREDIENTS: MICROCRYSTALLINE WAX; PETROLATUM; CASTOR OIL; LAURYL LAURATE; OLIVE OIL; HYDROGENATED CASTOR OIL; WHITE WAX; CARNAUBA WAX; CANDELILLA WAX; HYDROGENATED SOYBEAN OIL; GLYCERYL STEARATE SE; HIGH DENSITY POLYETHYLENE; GLYCERYL DIBEHENATE; .ALPHA.-TOCOPHEROL ACETATE, DL-; ASCORBYL PALMITATE; THIOCTIC ACID; QUERCETIN; CAESALPINIA SPINOSA RESIN; GLYCERIN

EltaMD UV Lip Balm SPF31

Warnings

For external use only Do not use on damaged or broken skin When using this product keep out of eyes Stop use and ask a physician if rash occurs Keep out of reach of children. If product is swallowed, get medical help or contact a Poison Control Center right away.

Active Ingredients

Octinoxate 7.5% Sunscreen

Zinc Oxide 9.0% Sunscreen

Uses

Helps prevent sunburn if used as directed with other sun protection measures (See Directions), decreases the risk of skin cancer and early skin aging caused by the sun.

Uses

Helps prevent sunburn if used as directed with other sun protection measures (See Directions), decreases the risk of skin cancer and early skin aging caused by the sun.

Directions

apply liberally 15 minutes before sun exposure reapply: after 80 minutes of swimming or sweating immediately after towel drying at lest every 2 hours Sun Protection Measures: Spending time in the sun increases your risk of skin cancer and early skin aging. To decrease this risk, regularly use a sunscreen with a broad-spectrum SPF of 15 or higher and other sun protection measures including: limit time int he sun, especially from 10 a.m. - 2 p.m. wear long-sleeve shirts, pants, hats and sunglasses children under 6 months: Ask a physician

Inactive Ingredients

Petrolatum, Ricinus Communis (Castor) Seed Oil, Cetearyl Alcohol, Lauryl Laurate, Purified Water, Flavor, Polyethylene, Hydrogenated Castor Oil, Olea Europaea (Olive) Fruit Oil, Cera Alba, Glycerin, Copernicia Cerifera (Carnauba) Wax, Glyceryl Behenate, Microcrystalline Wax, Quercetin, Thiotic Acid, Ascorbyl Palmitate, Tocopheryl Acetate, Euphorbia Cerifera (Candelilla) Wax, Hydrogenated Soybean Oil, Hydrolyzed Caesalpinia Spinosa Gum, Glyceryl Stearate, Caesalpinia Spinosa Gum

KEEP OUT OF REACH OF CHILDREN